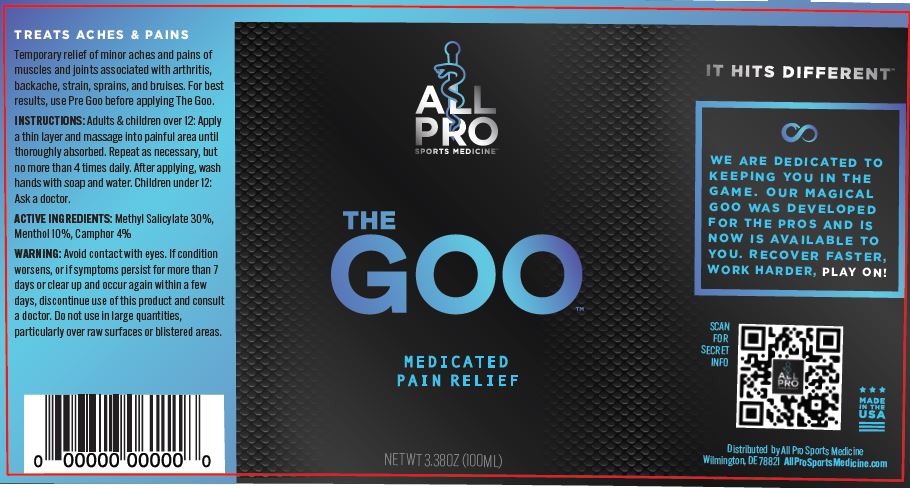 DRUG LABEL: THE GOO
NDC: 82503-101 | Form: GEL
Manufacturer: APSM PERFORMANCE, LLC
Category: otc | Type: HUMAN OTC DRUG LABEL
Date: 20260123

ACTIVE INGREDIENTS: METHYL SALICYLATE 30 g/100 mL; MENTHOL, UNSPECIFIED FORM 10 g/100 mL; CAMPHOR OIL 4 g/100 mL
INACTIVE INGREDIENTS: CAPRYLOYL GLYCERIN/SEBACIC ACID COPOLYMER (2000 MPA.S); XANTHAN GUM; CAPRYLHYDROXAMIC ACID; 1,2-HEXANEDIOL; PROPANEDIOL; DIMETHYL ISOSORBIDE; CARBOMER COPOLYMER TYPE B (ALLYL PENTAERYTHRITOL CROSSLINKED); STEARYL GLYCYRRHETINATE; FD&C YELLOW NO. 5 FREE ACID; FD&C GREEN NO. 3; STEARETH-2; FD&C BLUE NO. 1; WATER; STEARETH-21; STEARYL ALCOHOL; MENTHYL ETHYLAMIDO OXALATE; VANILLYL BUTYL ETHER; SODIUM HYDROXIDE

APSM - THE GOO (82503-101)

ACTIVE INGREDIENTS

Methyl Salicylate 30%

Menthol 10%

Camphor 4%

PURPOSE

TOPICAL PAIN RELIEF

USES

Temporary relief of minor aches and pains of muscles and joints associated with arthritis, backache, strain, sprains, and bruises.

WARNINGS

Avoid contact with eyes. If condition worsens, or if symptoms persist for more than 7 days or clear up and occur again within a few
days, discontinue use of this product and consult a doctor. Do not use in large quantities, particularly over raw surfaces or blistered areas.

KEEP OUT OF REACH OF CHILDREN.

INACTIVE INGREDIENTS

1,2-Hexanediol, Acrylates/C10-30 Alkyl Acrylate Crosspolymer, Caprylhydroxamic Acid, Capryloyl Glycerin/Sebacic Acid Copolymer, Dimethyl Isosorbide, Menthyl Ethylamido Oxalate, Propanediol, Steareth-2, Steareth-21, Stearyl Alcohol, Stearyl Glycyrrhetinate, Vanillyl Butyl Ether, Water, Xanthan Gum, Blue 1, Yellow 5, Green 3

DIRECTIONS

Adults and children over 12: Apply a thin layer and massage into painful area until thoroughly absorbed. Repeat as necessary, but no more than 4 times daily. After applying, wash hands with soap and water. Children under 12: Ask a doctor.